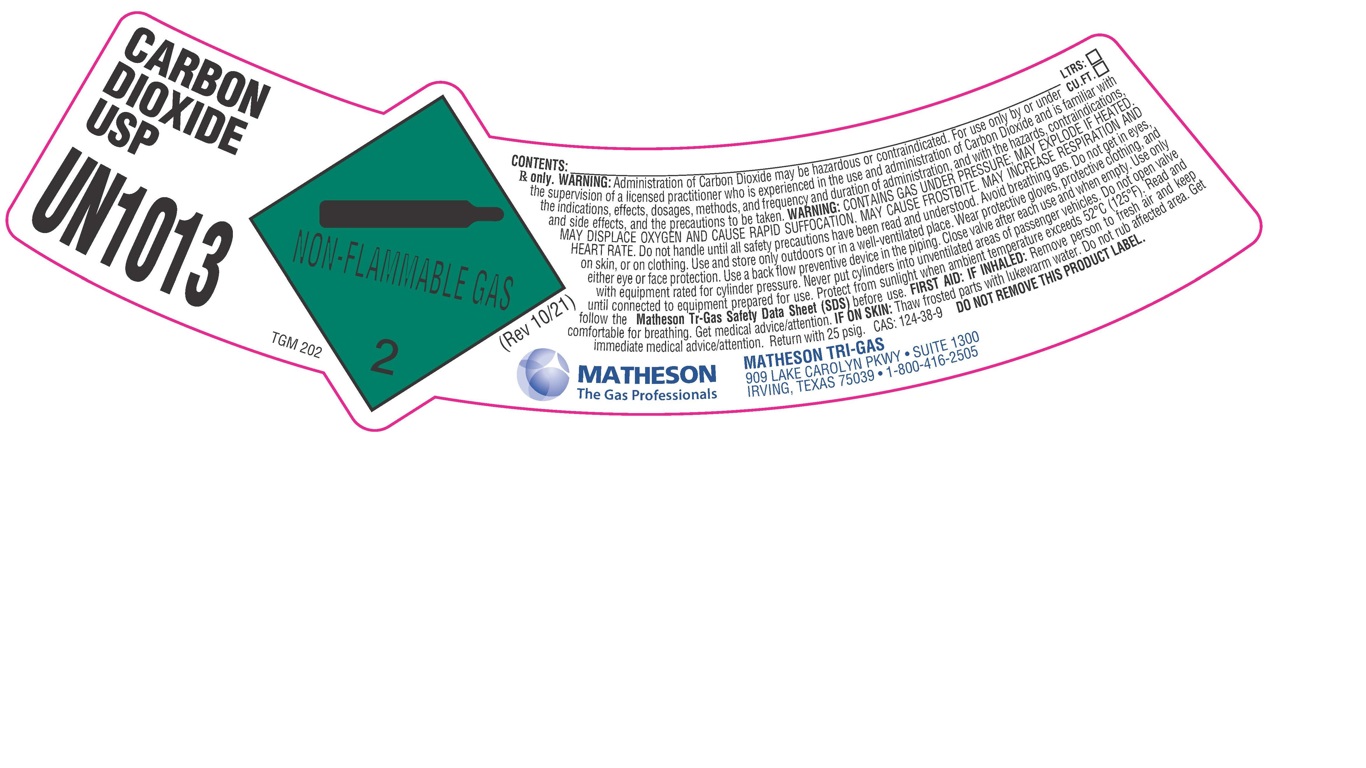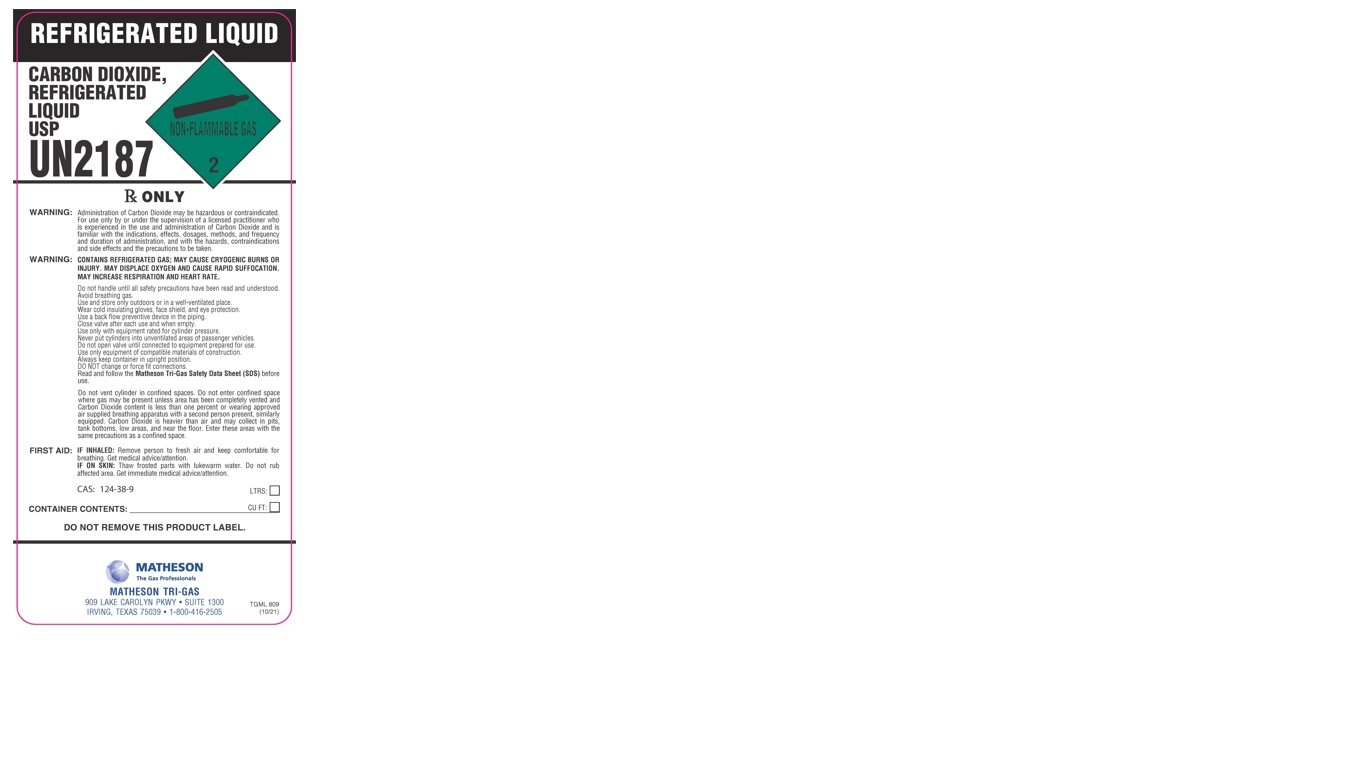 DRUG LABEL: Carbon Dioxide
NDC: 55037-402 | Form: GAS
Manufacturer: Matheson Tri-Gas, Inc.
Category: prescription | Type: HUMAN PRESCRIPTION DRUG LABEL
Date: 20251202

ACTIVE INGREDIENTS: CARBON DIOXIDE 992 mL/1 L

Carbon Dioxide

PACKAGE LABEL

CARBON DIOXIDE USP

UN1013

CONTENTS: LTRS: CU.FT.

Rx only. WARNING: Administration of Carbon Dioxide may be hazardous or contraindicated. For use only by or under the supervision of a licensed practitioner who is experienced in the use and administration of Carbon Dioxide and is familiar with the indications, effects, dosages, methods, and frequency and duration of administration, and with the hazards, contraindications, and side effects, and the precautions to be taken. WARNING: CONTAINS GAS UNDER PRESSURE; MAY EXPLODE IF HEATED. MAY DISPLACE OXYGEN AND CAUSE RAPID SUFFOCATION. MAY CAUSE FROSTBITE. MAY INCREASE RESPIRATION AND HEART RATE. Do not handle until all safety precautions have been read and understood. Avoid breathing gas. Do not get in eyes, on skin, or on clothing. Use and store only outdoors or in a well-ventilated place. Wear protective gloves, protective clothing, and either eye or face protection. Use a back flow preventive device in the piping. Close valve after each use and when empty. Use only with equipment rated for cylinder pressure. Never put cylinders into unventilated areas of passenger vehicles. Do not open valve until connected to equipment prepared for use. Protect from sunlight when ambient temperature exceeds 52 C (125 F). Read and follow the Matheson Tri-Gas Safety Data Sheet (SDS) before use. FIRST AID: IF INHALED: Remove person to fresh air and keep comfortable for breathing. Get medical advice/attention. IF ON SKIN: Thaw frosted parts with lukewarm water. DO not rub affected area. Get immediate medical advice/attention. Return with 25 psig. CAS: 124-38-9 DO NOT REMOVE THIS PRODUCT LABEL.

MATHESON The Gas Professionals

MATHESON TRI-GAS

909 LAKE CAROLYN PKWY. SUITE 1300

IRVING, TEXAS 75039 . 1-800-416-2505

PACKAGE LABEL

REFRIGERATED LIQUID

CARBON DIOXIDE, REFRIGERATED LIQUD USP

UN2187

Rx ONLY

WARNING: Administration of Carbon Dioxide may be hazardous or contraindicated. For use only by or under the supervision of a licensed practitioner who is experienced in the use and administration of Carbon Dioxide and is familiar with the indications, effects, dosages, methods, and frequency and duration of administration, and with the hazards, contraindications and side effects and the precautions to be taken.

WARNING: CONTAINS REFRIGERATED GAS; MAY CAUSE CRYOGENIC BURNS OR INJURY. MAY DISPLACE OXYGEN AND CAUSE RAPID SUFFOCATION. MAY INCREASE RESPIRATION AND HEART RATE.

Do not handle until all safety precautions have been read and understood. Avoid breathing gas. Use and store only outdoors or in a well-ventilated place. Wear cold insulating gloves, face shield, and eye protection. Use a back flow preventive device in the piping. Close valve after each use and when empty. Use only with equipment rated for cylinder pressure. Never put cylinders into unventilated areas of passenger vehicles. Do not open valve until connected to equipment prepared for use. Use only equipment of compatible materials of construction. Always keep container in upright position. DO NOT change or force fit connections. Read and follow the Matheson Tri-Gas Safety Data Sheet (SDS) before use.

Do not vent cylinder in confined spaces. Do not enter confined space where gas may be present unless area has been completely vented and Carbon Dioxide content is less than one perfect or wearing approved air supplied breathing apparatus with a second person present, similarly equipped. Carbon Dioxide is heavier than air and may collect in pits, tank bottoms, low areas, and near the floor. Enter these areas with the same precautions as a confined space.

FIRST AID: IF INHALED: Remove person to fresh air and keep comfortable for breathing. Get medical advice/attention.

IF ON SKIN: Thaw frosted parts with lukewarm water. Do not rub affected area. Get immediate medical advice/attention.

CAS: 124-38-9

CONTAINER CONTENTS: LTRS: CU FT:

DO NOT REMOVE THIS PRODUCT LABEL.

MATHESON The Gas Professionals

MATHESON TRI-GAS

909 LAKE CAROLYN PKWY. SUITE 1300

IRVING, TEXAS 75039 . 1-800-416-2505